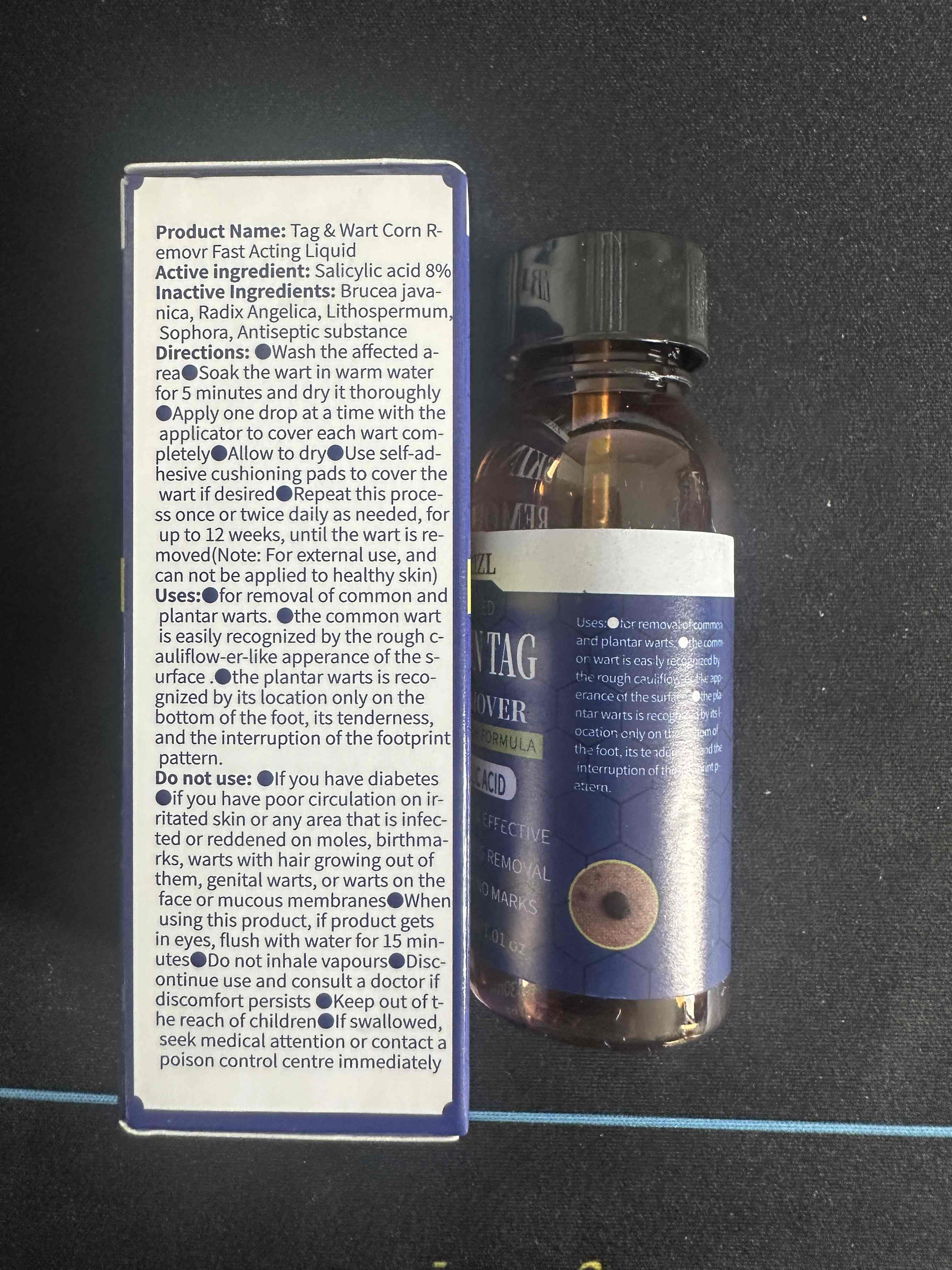 DRUG LABEL: Tag  Wart Corn R-emovr Fast Acting Liquid
NDC: 85593-001 | Form: LIQUID
Manufacturer: Guangzhou ChuanMa International Trading Co.,Ltd.
Category: otc | Type: HUMAN OTC DRUG LABEL
Date: 20250715

ACTIVE INGREDIENTS: SALICYLIC ACID 8 g/100 mL
INACTIVE INGREDIENTS: LITHOSPERMUM CANESCENS WHOLE; ANGELICA BISERRATA WHOLE; SOPHORA FLAVESCENS ROOT; BRUCEA JAVANICA FRUIT; LISTERIA MONOCYTOGENES

ACTIVE INGREDIENT

Salicylic acid 8%

PURPOSE

skin tag remover

WHEN USING

for removal of common andplantarwarts.

the common wartis easily recognized by the rough cauliflow-er-like apperance of the s-urface .

the plantar warts is recognized by its location only on thebottom of the foot, its tenderness,and the interruption of the footprintpattern.

DO NOT USE

@lfyou have diabetes@if you have poor circulation on irritated skin or any area that is infected or reddened on moles, birthma.rks, warts with hair growing out ofthem, genital warts, or warts on theface ormucous membranes@Whenusing this product, if product getsin eyes,flush with water for 15 minuteseDo not inhale vapours@Discontinue use and consult a doctor ifdiscomfort persists @Keep out of t.he reach of children@lfswallowed,seek medical attention or contact apoison control centre immediately

WARNINGS

For external use only - When using this product - skin irritation and dryness may occur if you use other topical acne medications at the same time or immediately following use of this product.

INDICATIONS AND USAGE

Directions:@Wash the affected a-rea@Soak the wart in warm waterfor 5 minutes and dry it thoroughly@Apply one drop at a time with theapplicator to cover each wart completely@Allow to dry@Use self-ad-hesive cushioning pads to cover thewart if desired@Repeat this proce-ss once or twice daily as needed, foup to 12 weeks, until the wart is removed(Note: For external use, andcan not be applied to healthy skin)

Keep out of reach of children.
If swallowed, get medial help or contact a Poison Control Center right away.

INACTIVE INGREDIENT

Inactive Ingredients: Brucea java.nica, Radix Angelica, LithospermumSophora,Antiseptic substance

DOSAGE AND ADMINISTRATION

@Wash the affected a-rea@Soak the wart in warm waterfor 5 minutes and dry it thoroughlyDApply one drop at a time with theapplicator to cover each wart com-pletely@Allow to dry@Use self-ad-hesive cushioning pads to cover thewart if desired@Repeat this process once or twice daily as needed, forup to 12 weeks,